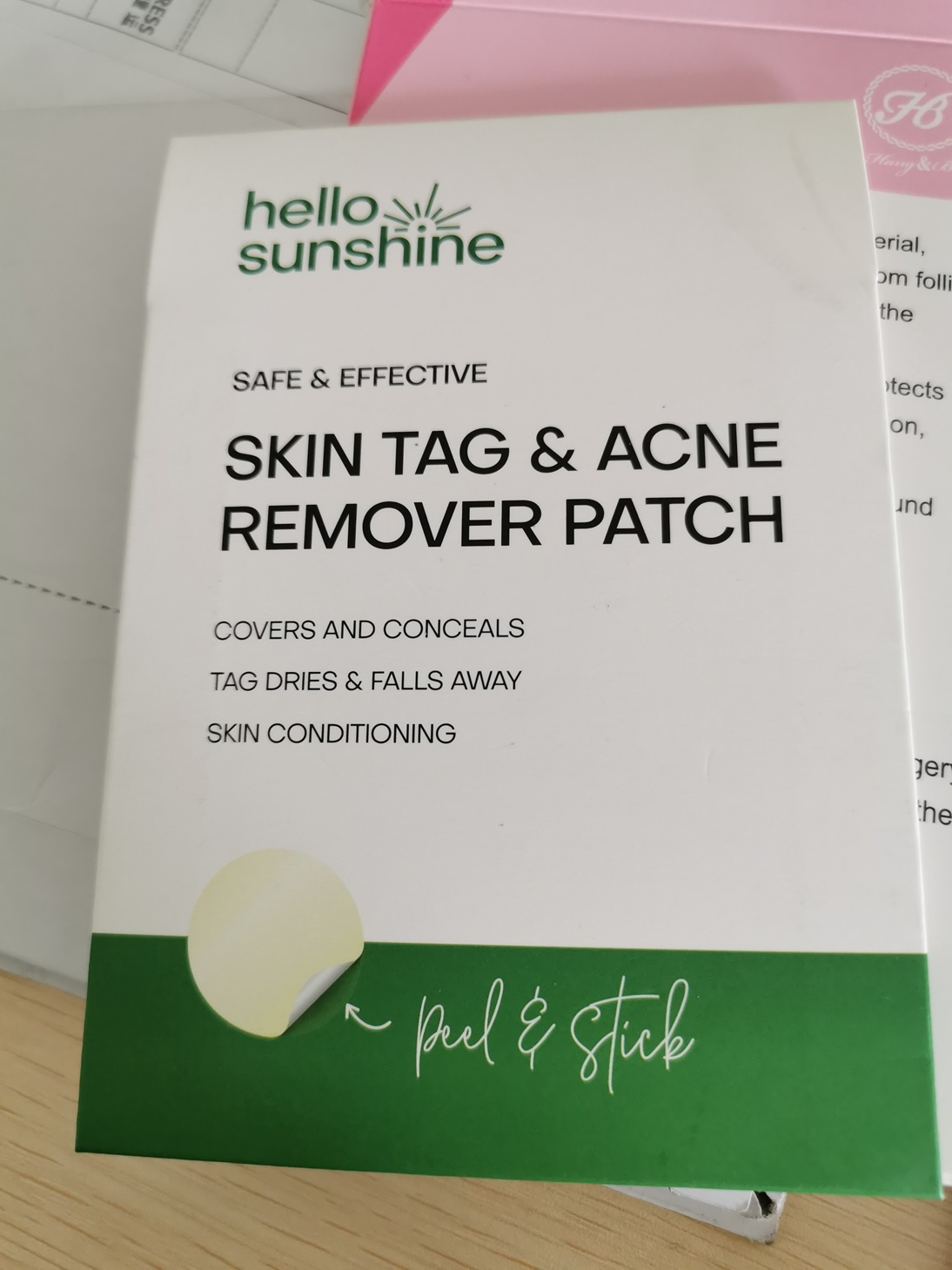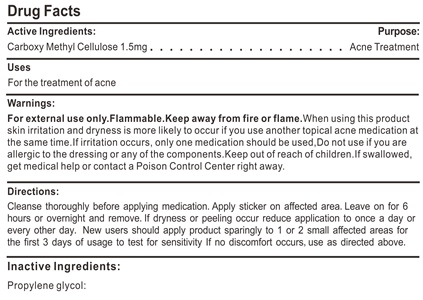 DRUG LABEL: ACNE PATCHS
NDC: 81400-101 | Form: PATCH
Manufacturer: Shenzhen Xing Ji Zhi Tong Technology Co.,Ltd
Category: otc | Type: HUMAN OTC DRUG LABEL
Date: 20210106

ACTIVE INGREDIENTS: CARBOXYMETHYLCELLULOSE 1.5 mg/1 1
INACTIVE INGREDIENTS: PROPYLENE GLYCOL

ACNE PATCH

ACNE PATCH

Active Ingredient(s)

CARBOXYMETHYLCELLULOSE 1.5mg/patch. Purpose: Acne Treatment

Purpose

ACNE PATCH, Acne Treatment

Use

For the treatment pf acne.

Warnings

For external use only. Flammable. Keep away from heat or flame

Do not use

- in children less than 2 months of age

When using this product, skin irritation and dryness is more likely to occur if you use another topical acne medication at the same time.

If irritation occurs, only one medication should be used. Do not use if you are allergic to the dressing or any of the components.

Keep out of reach of children. If swallowed, get medical help or contact a Poison Control Center right away.

Stop use and ask a doctor if irritation or rash occurs. These may be signs of a serious condition.

Keep out of reach of children. If swallowed, get medical help or contact a Poison Control Center right away.

Directions

- Cleanse thoroughly before applying medication. Apply sticker on affected area. Leave on for 6 hours or overnight and remove. If dryness or peeling occur reduce application to once a day or every other day. New users should apply product sparingly to 1 or 2 small affected areas for the first 3 days of usage to test for sensitivity if no discomfort occurs, use a directed above.

Other information

- Store between 15-30C (59-86F)
- Avoid freezing and excessive heat above 40C (104F)

Inactive ingredients

Propylene glycol